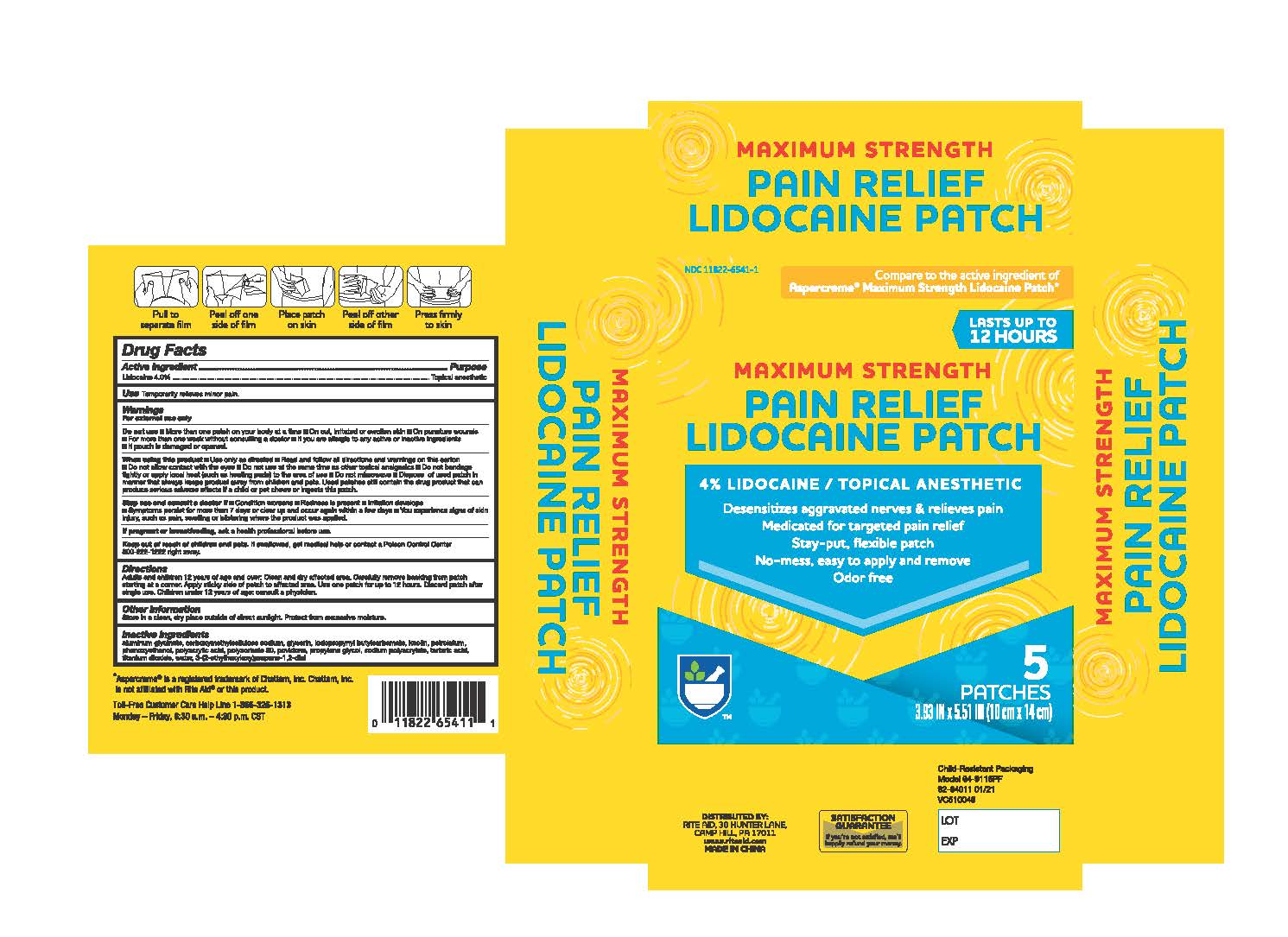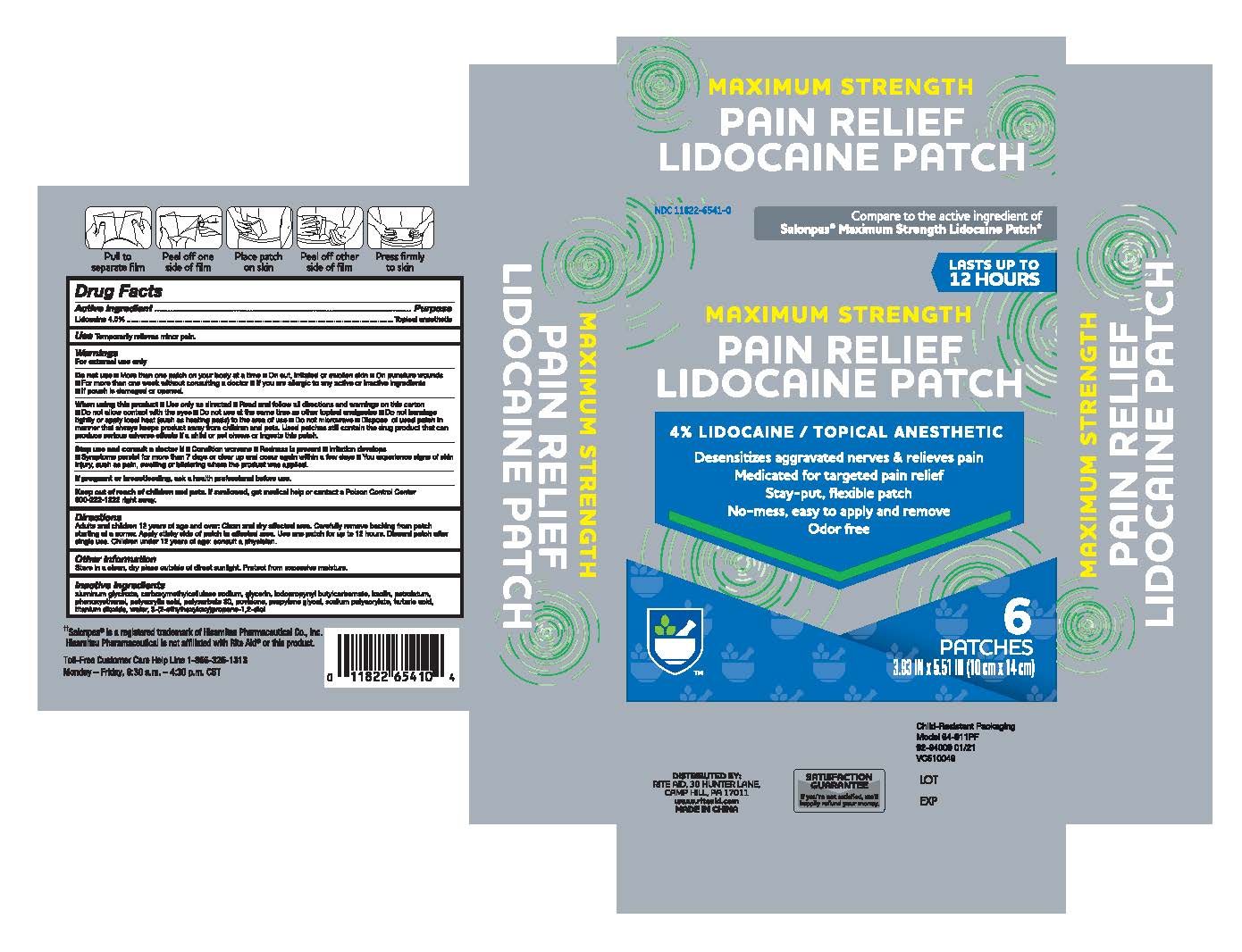 DRUG LABEL: Maximum Strength Pain Relief Lidocaine Patch
NDC: 11822-6541 | Form: PATCH
Manufacturer: Rite Aid Corporation
Category: otc | Type: HUMAN OTC DRUG LABEL
Date: 20241218

ACTIVE INGREDIENTS: LIDOCAINE 4 g/100 g
INACTIVE INGREDIENTS: POLYACRYLIC ACID (8000 MW); PETROLATUM; CARBOXYMETHYLCELLULOSE SODIUM; DIHYDROXYALUMINUM AMINOACETATE; GLYCERIN; KAOLIN; ETHYLHEXYLGLYCERIN; PHENOXYETHANOL; POLYSORBATE 80; POLYETHYLENE GLYCOL 400; POVIDONE, UNSPECIFIED; SODIUM POLYACRYLATE (8000 MW); TARTARIC ACID; TITANIUM DIOXIDE; WATER; IODOPROPYNYL BUTYLCARBAMATE

Maximum Strenght Pain Relief Lidocaine Patch

Active Ingredients

Lidocaine 4% . . . . . . . . . . . . . . . . . . . . . . . . . . . . . . Topical Anesthetic

Warnings

For external use only.

Do not Use

■ more than one patch on your body at a time

■ on cut, irritated or swollen skin

■ on puncture wounds

■ for more than one week without consulting a doctor

■ if you are allergic to any active or inactive ingredients

■ if pouch is damaged or opened.

When using this product

■ use only as directed

■ read and follow all directions and warnings on this carton

■ do not allow contact with the eyes

■ do not use at the same time as other topical analgesics

■ do not bandage tightly or apply local heat (such as heating pads) to the area of use

■ do not microwave

■ dispose of used patch in manner that always keeps product away from children and pets. Used patches still contain the drug product that can produce serious adverse effects if a child or pet chews or ingests this patch.

Stop use and consult a doctor

■ condition worsens

■ redness is present

■ irritation develops

■ symptoms persist for more than 7 days or clear up and occur again within a few days

■ you experience signs of skin injury, such as pain, swelling or blistering where the product was applied.

Keep out of reach of children and pets.

If swallowed, get medical help or contact a Poison Control Center 800-222-1222 right away.

Dosage and Administration

Directions Adults and children 12 years of age and over :

■ Clean and dry affected area

■ Carefully remove backing from patch starting at a corner.

■ Apply sticky side of patch to affected area.

■ use one patch for up to 12 hours.

■ Discard patch after single use.

■Children under 12 years of age: consult a physician.

PREGNANCY OR BREAST FEEDING

If pregnant or breastfeeding, ask a health professional before use.

Other Safety Information

Store in a clean, dry place outside of direct sunlight. Protect from excessive moisture.

Inactive Ingredients

Aluminum Glycinate, carboxymethylcellulose sodium, Glycerin, iodopropynyl butylcarbamate, Kaolin, petrolatum, phenoxyethanol, polyacrylic acid, Polysorbate 80, Povidone, Propylene Glycol, Sodium Polyacrylate, Tartaric Acid, Titanium Dioxide, Water, 3-(2-ethylhexyloxy)propane-1,2-diol

Uses

Temporarily relieves minor pain.

Uses

Temporarily relieves minor pain.